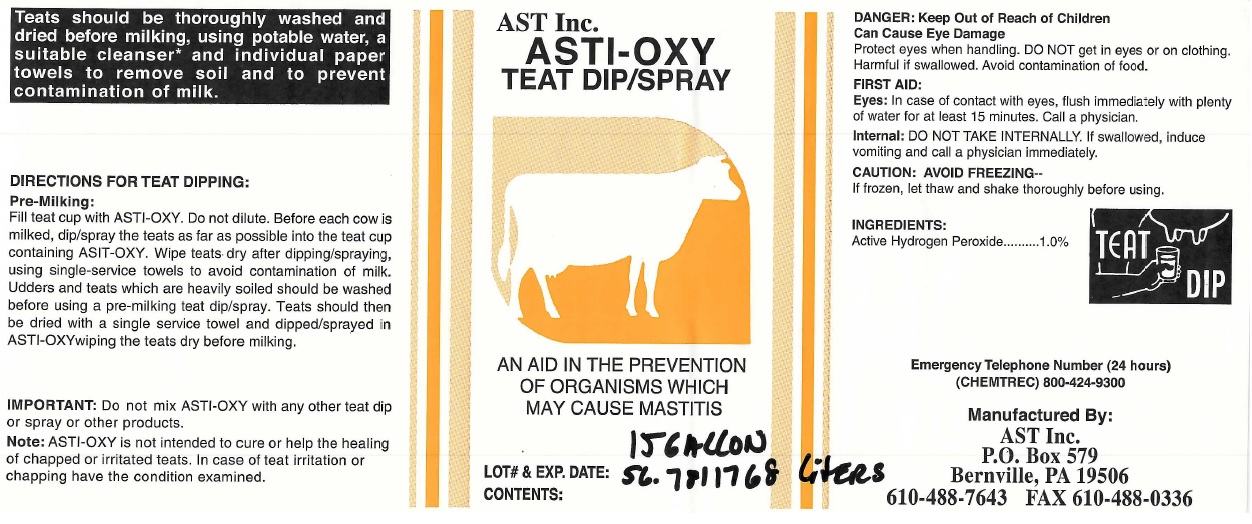 DRUG LABEL: AST Inc. ASTI-OXY TEAT DIP
NDC: 52657-0101 | Form: SOLUTION
Manufacturer: Advanced Skin Technologies Inc.
Category: animal | Type: OTC ANIMAL DRUG LABEL
Date: 20220218

ACTIVE INGREDIENTS: HYDROGEN PEROXIDE 10 mg/0.001 L

AST Inc. ASTI-OXY TEAT DIP/SPRAY

DANGER:

Can Cause Eye Damage

Protect eyes when handling. DO NOT get in eyes or on clothing, Harmful if swallowed. Avoid contamination of food.

FIRST AID:

Eyes: In case of contact with eyes, flush immediately with plenty of water for at least 15 minutes. Call a physician.

Internal: DO NOT TAKE INTERNALLY. If swallowed, induce vomiting and call a physician immediately.

CAUTION : AVOID FREEZING--

If frozen, let thaw and shake thoroughly before using.

INGREDIENTS:

Active Hydrogen Peroxide 1.0%

Teats should be thoroughly washed and dried before milking, using potable water, a suitable cleanser* and individual paper towels to remove soil and to prevent contamination of milk.

DIRECTIONS FOR TEAT DIPPING:

Pre-Milking:

Fill teat cup with ASTI-OXY. Do not dilute. Before each cow is milked, dip/spray the teats as far as possible into the teat cup containing ASIT-OXY. Wipe teats dry after dipping/spraying, using single-service towels to avoid contamination of milk. Udders and teats which are heavily soiled should be washed before using a pre-milking teat dip/spray. Teats should then be dried with a single service towel and dipped/sprayed in AST-OXY wiping the teats dry before milking.

IMPORTANT:

Do not mix ASTI-OXY with any other teat dip or spray or other products.

Note:ASTI-OXY is not intended to cure or help the healing of chapped or irritated teats. In case of teat irritation or chapping have the condition examined.